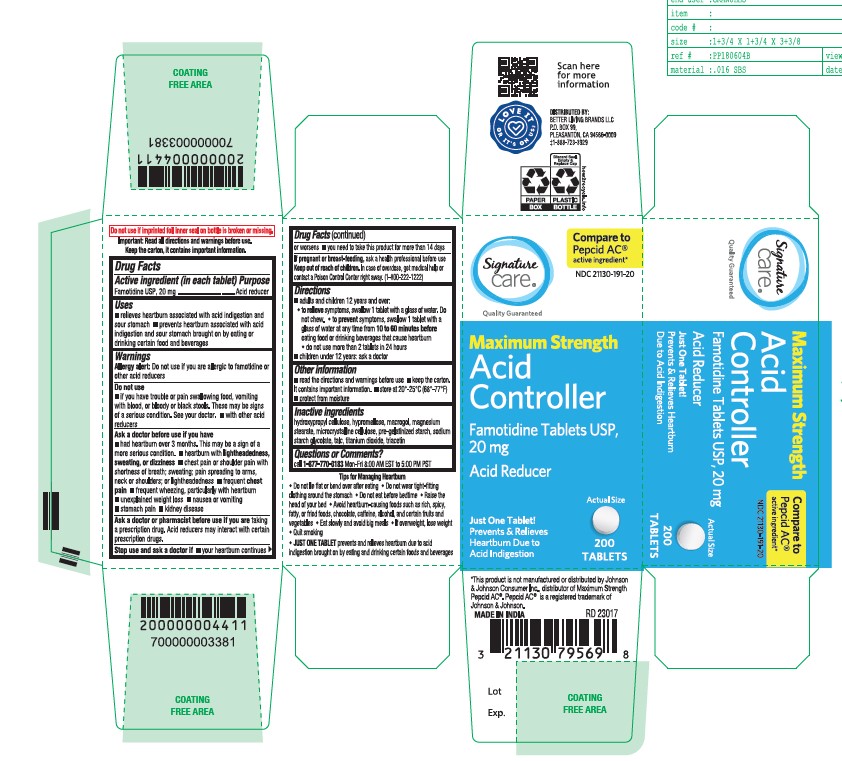 DRUG LABEL: Famotidine
NDC: 21130-191 | Form: TABLET
Manufacturer: SAFEWAY
Category: otc | Type: HUMAN OTC DRUG LABEL
Date: 20251218

ACTIVE INGREDIENTS: FAMOTIDINE 20 mg/1 1
INACTIVE INGREDIENTS: TITANIUM DIOXIDE; MICROCRYSTALLINE CELLULOSE; SODIUM STARCH GLYCOLATE TYPE A; MAGNESIUM STEARATE; TALC; HYDROXYPROPYL CELLULOSE (110000 WAMW); TRIACETIN; STARCH, CORN; HYPROMELLOSE 2910 (6 MPA.S); POLYETHYLENE GLYCOL 4000

Maximum Strength
Acid Controller
Famotidine Tablets USP, 20mg
Acid Reducer
Just one Tablet!
Prevents & Relieves Heartburn due to acid indigestion

Active Ingredient (in each tablet)

Famotidine Tablets USP, 20mg

Purpose

Acid Reducer

Uses

- relieves heartburn associated with acid indigestion and sour stomach
- prevents heartburn associated with acid indigestion and sour stomach brought on by eating or drinking certain food and beverages

Allergy alert

Do not use if you are allergic to famotidine or other acid reducers

Do not use

- if you have trouble or pain swallowing food, vomitiing with blood, or bloody or black stools. These may be signs of a serious condition. See your doctor.
- with other acid reducers

Ask a doctor before use if you have

- had heartburn over 3 months. This may be a sign of a more serious condition.
- heartburn with lighteasdedness, sweating or dizziness
- chest pain or shoulder pain with shortness of breath; sweating; pain spreading to arms, neck or shoulders; or lightheadedness
- frequent chestpain
- frequent wheezing, particularly with heartburn
- unexplained weight loss
- nausea or vomiting
- stomach pain
- kidney disease

Ask a doctor or pharmacist before use if you are

taking a prescription drug. Acid reducers may interact with certain prescription drugs.

Stop use and ask a doctor if

- your heartburn continues or worsens
- you need to take this product for more than 14 days

If pregnant or breast-feeding,

ask a health professional before use

Keep out of reach of children

In case of overdose, get medical help or contact a poison control center right away. (1-800-222-1222)

Directions

- adults and children 12 years and over:
- to relieve symptoms, swallow 1 tablet with a glass of water. Do not chew.
- to prevent symptoms, swallow 1 tablet with a glass of water at any time from 10 to 60 minutes before eating food or drinking beverages that cause heartburn.
- do not use more than 2 tablets in 24 hours
- children under 12 years: ask a doctor

Other Information

- read the directions and warnings before use
- keep the carton. It contains important information.
- store at 20-25 C (68-77F)
- protect from moisture

Inactive Ingredients

hydroxypropyl cellulose, hypromellose, macrogol, magnesium stearate, microcrystalline cellulose, pre-gelatinized starch, sodium
starch glycolate, talc, titanium dioxide, triacetin

Questions or Comments?

call 1-877-770-3183 Mon-Fri 8:00 AM EST to 5:00 PM PST